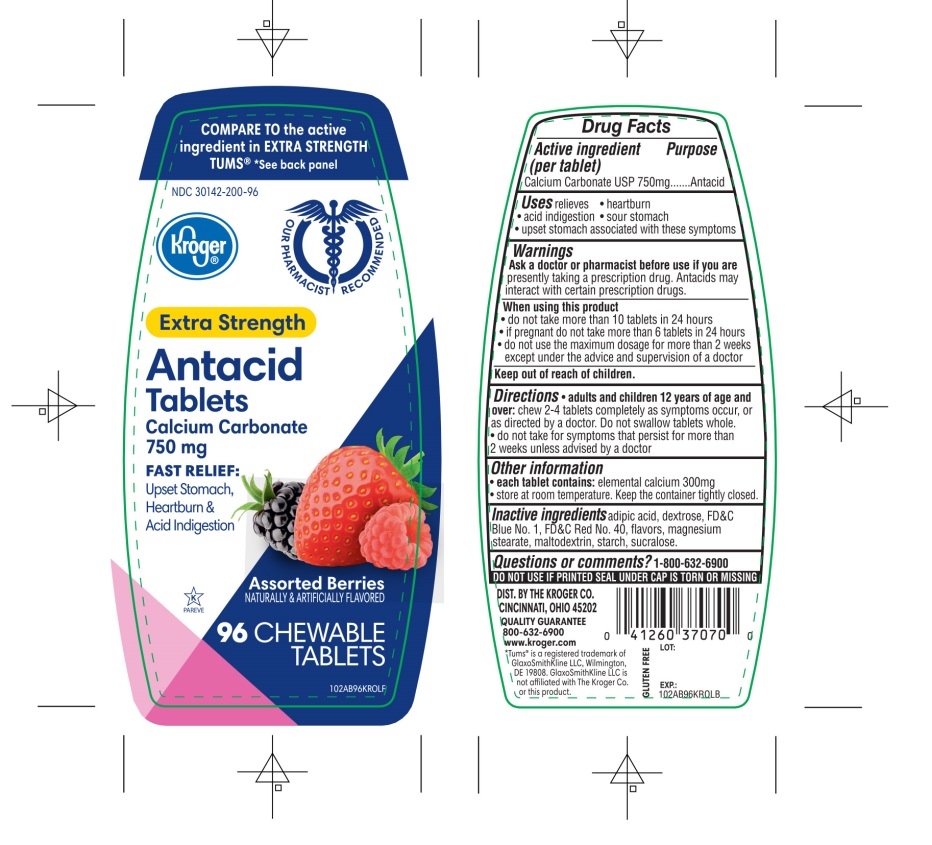 DRUG LABEL: Kroger Extra Strength

NDC: 30142-200 | Form: TABLET, CHEWABLE
Manufacturer: KROGER COMPANY
Category: otc | Type: HUMAN OTC DRUG LABEL
Date: 20250801

ACTIVE INGREDIENTS: CALCIUM CARBONATE 750 mg/1 1
INACTIVE INGREDIENTS: ADIPIC ACID; DEXTROSE, UNSPECIFIED FORM; FD&C BLUE NO. 1; FD&C RED NO. 40; MAGNESIUM STEARATE; MALTODEXTRIN; STARCH, CORN; SUCRALOSE

Kroger Extra Strength Antacid Calcium Drug Facts

Active ingredient (per tablet)

Calcium Carbonate USP 750mg

Purpose

Antacid

Uses

relieves

- heartburn
- acid indigestion
- sour stomach
- upset stomach associated with these symptoms

Warnings

Ask a doctor or pharmacist before use if you arepresently taking a prescription drug. Antacids may interact with certain prescription drugs.

When using this product

- do not take more than 10 tablets in 24 hours
- if pregnant do not take more than 6 tablets in 24 hours
- do not use the maximum dosage for more than 2 weeks except under the advice and supervision of a doctor.

Directions

- adults and children 12 years of age and over:chew 2-4 tablets completely as symptoms occur, or as directed by a doctor. Do not swallow tablets whole.
- do not take for symptoms that persist for more than 2 weeks unless advised by a doctor

Other information

- each tablet contains:elemental calcium 300mg
- store at room temperature. Keep the container tightly closed.
  Safety sealed: DO NOT USE IF PRINTED SEAL UNDER CAP IS TORN OR MISSING

Inactive ingredients

adipic acid, dextrose, FD&C blue No. 1, FD&C Red No. 40, flavors, magnesium stearate, maltodextrin, starch, sucralose.

Questions?

1-800-632-6900

Package/Label Principal Display Panel

NDC # 30142-200-96

Kroger®

COMPARE TO active ingredient in EXTRA STRENGTH TUMS® see back panel

OUR PHARMACISTS RECOMMEND

EXTRA STRENGTH

Antacid Tablets

Calcium Carbonate 750 mg

FAST RELIEF:

Upset Stomach, Heartburn & Acid Indigestion

Assorted Berry

NATURALLY & ARTIFICIALLY FLAVORED

96 CHEWABLE TABLETS

GLUTEN- FREE

K PAREVE

QUALITY GUARANTEED-

DISTRIBUTED BY:

THE KROGER CO.

CINCINNATI,

OHIO 45202

800-632-6900 www.kroger.com

TUMS® is a registered trademark of GlaxoSmithKline LLC, Wilmington, DE 19808. GlaxoSmithKline LLC is not affiliated with The Kroger Co. or this product.